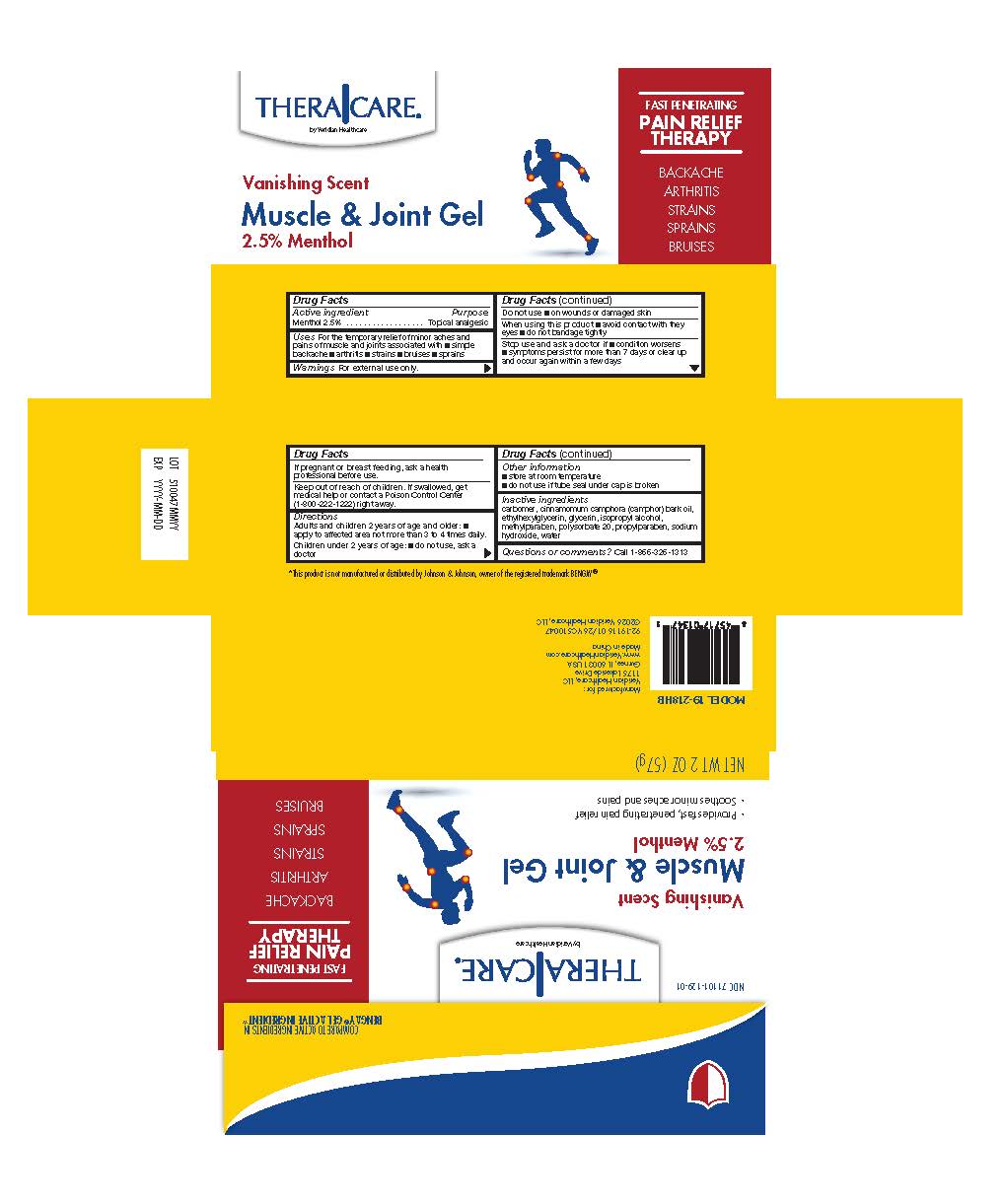 DRUG LABEL: TheraCare Muscle and Joint Gel
NDC: 71101-129 | Form: GEL
Manufacturer: Veridian Healthcare
Category: otc | Type: HUMAN OTC DRUG LABEL
Date: 20260126

ACTIVE INGREDIENTS: MENTHOL 2.5 g/100 g
INACTIVE INGREDIENTS: PROPYLPARABEN; METHYLPARABEN; ETHYLHEXYLGLYCERIN; CAMPHOR OIL; CARBOMER HOMOPOLYMER TYPE C (ALLYL PENTAERYTHRITOL CROSSLINKED); ISOPROPYL ALCOHOL; WATER; SODIUM HYDROXIDE; GLYCERIN; POLYSORBATE 20

TheraCare Muscle & Joint Gel

Drug Facts

Active Ingredient

Menthol 2.5%

Purpose

- Topical Analgesic

Uses

Temporary relief from minor aches and pains of sore muscles and joints associated with:

■ simple backache

■arthritis

■strains

■bruises

■sprains

Warnings

For external use only

Do not use

On wounds or damage skin

When using this product, do not

When using this product:

■ avoid contact with eyes

■do not bandage tightly

Stop use and ask a doctor if: the condition worsens, or if symptoms persist for more than 7 days or clear up and occur again withing a few days.

PREGNANCY OR BREAST FEEDING

If pregnant or breast-feeding,ask a health professional before use.

Keep out of reach of children. In case of accidental ingestion, get medical help orcontact a Poison Control Center (800-222-1222) right away.

Directions

- Adults and children 2 years of age and older apply to the affected area not more than 3 to 4 times daily
- Children under 2 years of age: do not use, ask a doctor

Other information

- store at room temperature
- do not use if tube seal under cap is broken

Inactive ingredients

carbomer, cinnamomum camphora (camphor) bark oil, ethylhexylglycerin, glycerin, isopropyl alcohol, methylparaben, polysorbate 20, propylparaben, sodium hydroxide, water